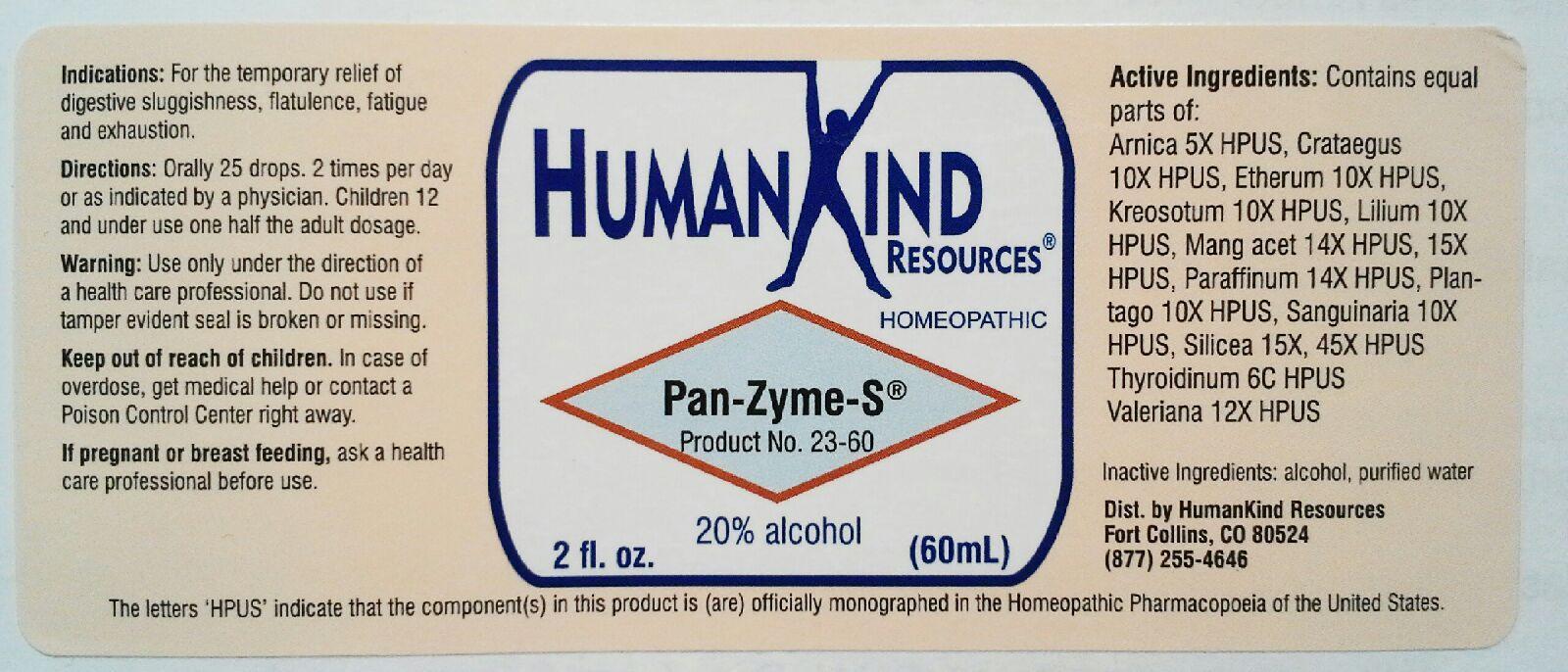 DRUG LABEL: Pan-Zyme-S
NDC: 64616-101 | Form: LIQUID
Manufacturer: Vitality Works, Inc.
Category: homeopathic | Type: HUMAN OTC DRUG LABEL
Date: 20251217

ACTIVE INGREDIENTS: ARNICA MONTANA ROOT 5 [hp_X]/1 mL; CRATAEGUS FRUIT 10 [hp_X]/1 mL; ETHER 10 [hp_X]/1 mL; WOOD CREOSOTE 10 [hp_X]/1 mL; LILIUM LANCIFOLIUM WHOLE FLOWERING 10 [hp_X]/1 mL; MANGANESE ACETATE TETRAHYDRATE 15 [hp_X]/1 mL; PARAFFIN 14 [hp_X]/1 mL; PLANTAGO MAJOR 10 [hp_X]/1 mL; SANGUINARIA CANADENSIS ROOT 10 [hp_X]/1 mL; SILICON DIOXIDE 45 [hp_X]/1 mL; THYROID, UNSPECIFIED 6 [hp_C]/1 mL; VALERIAN 12 [hp_X]/1 mL
INACTIVE INGREDIENTS: ALCOHOL; WATER

Pan-Zyme-S

Pan-Zyme-S

Arnica Montana 5X Paraffinum 14X

Crataegus Oxyacantha 10X Plantago Major 10X

Etherum 10X Sanguinaria Canadensis 10X

Kreosotum 10X Silicea 15X, 45X

Lilium Tigrinum 10X Thyroidiunm 6C

Manganum Aceticum 14X, 15X Valeriana Officinalis 12X

Pan-Zyme-S

Alcohol, Purified Water

Pan-Zyme-S

Use only under the direction of a health care professional. Do not use if tamper evident seal is broken or missing.

Pan-Zyme-S

Keep out of reach of children. In case of overdose, get medical help or contact a Poison Control Center right away.

Pan-Zyme-S

For the temporary relief of digestive sluggishness, flatulence, fatigue and exhaustion.

Pan-Zyme-S

Orally 25 drops, 2 times per day or as indicated by a physician. Do not use if tamper evident seal is broken.

Pan-Zyme-S

Gives energy and support to the pancreas to boost functional levels, to increase and balance its enzymatic output, to aid in normalizaion of metabolic and digestive functions